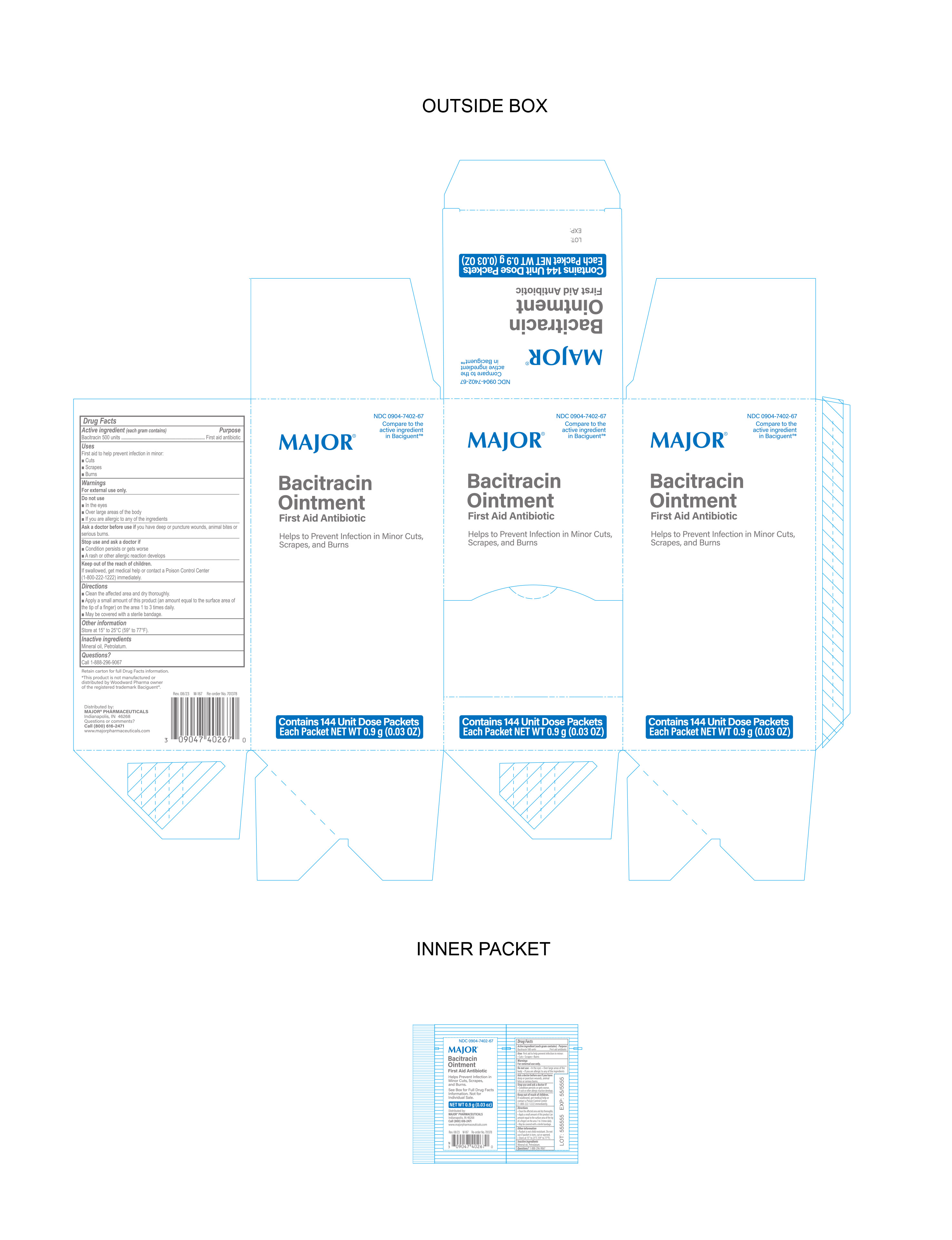 DRUG LABEL: Major Bacitracin
NDC: 0904-7402 | Form: OINTMENT
Manufacturer: Major Pharmaceuticals
Category: otc | Type: HUMAN OTC DRUG LABEL
Date: 20240308

ACTIVE INGREDIENTS: BACITRACIN 500 [USP'U]/1 g
INACTIVE INGREDIENTS: PETROLATUM; MINERAL OIL

Major Bacitracin Ointment

Active Ingredient

Bacitracin 500 Units per gram

Purpose

First Aid Antibiotic

Uses

First Aid to help prevent infection in minor

- cuts
- scrapes
- burns

Warnings

For External Use Only.

Do Not Use

- in eyes
- over large areas of the body
- if you are allergic to any of the ingredients

Ask Doctor before Use

if you have deep or puncture wounds, animal bites or serious burns.

Stop Use and Ask Doctor if

- The condition persists or gets worse
- A rash or allergic reaction develops

Directions

- Clean the affected area and dry thoroughly
- Apply a small amount of the product (an amount equal to the surface area of the tip of a finger) on the area 1 to 3 times daily
- May be covered with a sterile bandage

Inactive Ingredients

mineral oil, petrolatum

Questions

Call 1-888-296-9067

Storage Information

Store at 15° to 25°C (59° to 77°F).

Keep out of reach of children

If swallowed, get medical help or contact a Poison Control Center (1-800-222-1222) immediately.

Other Information

Distributed By:

MAJOR® PHARMACEUTICALS

Indianapolis, IN 46268

Call (800) 616-2471

www.majorpharmaceuticals.com

This product is not manufactured or distributed by Woodward Pharma woner of the registered trademark Baciguent®